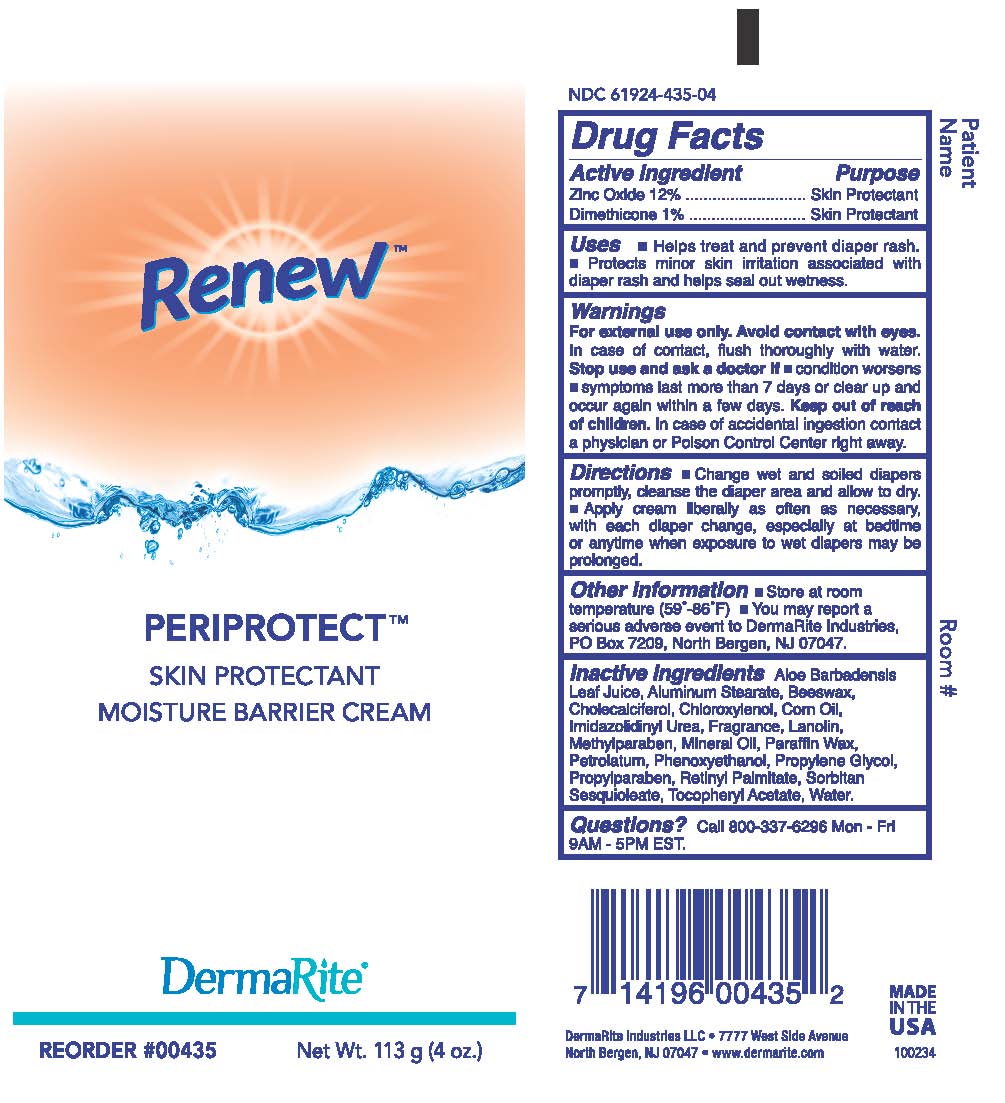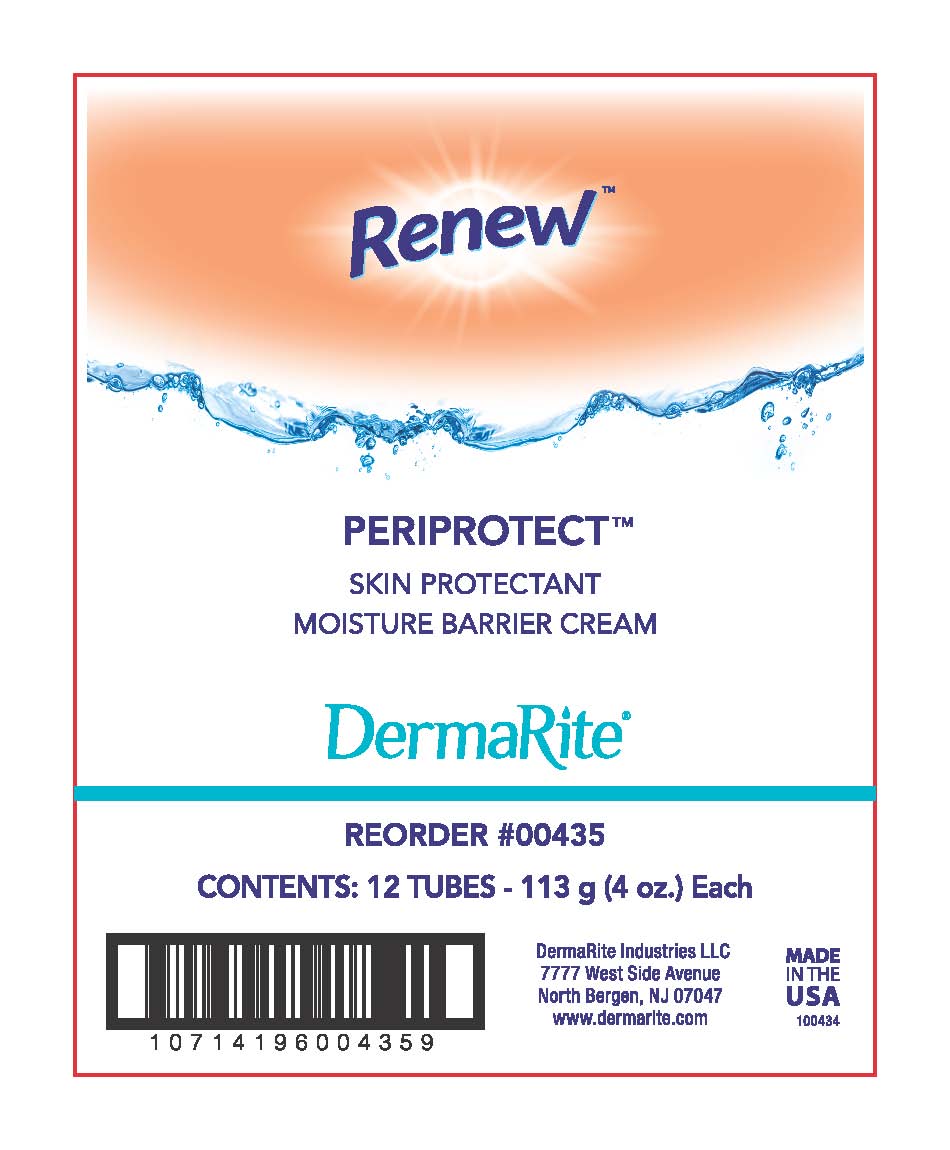 DRUG LABEL: Renew Periprotect
NDC: 61924-435 | Form: OINTMENT
Manufacturer: DermaRite Industries, LLC
Category: otc | Type: HUMAN OTC DRUG LABEL
Date: 20241205

ACTIVE INGREDIENTS: ZINC OXIDE 12 g/100 g; DIMETHICONE 1 g/100 g
INACTIVE INGREDIENTS: PETROLATUM; 2-PHENYLPROPANAL PROPYLENE GLYCOL ACETAL; VITAMIN A PALMITATE; TOCOPHERYL RETINOATE; WATER; N-(1,3,4-TRIS(HYDROXYMETHYL)-2,5-DIOXO-4-IMIDAZOLIDINYL)-N,N'-BIS(HYDROXYMETHYL)UREA; MINERAL OIL; PARAFFIN; CHOLECALCIFEROL; ALOE VERA LEAF POLYSACCHARIDES; ALUMINUM STEARATE; YELLOW WAX; CORN OIL; PHENOXYETHANOL; PROPYLPARABEN; SORBITAN SESQUIOLEATE; METHYLPARABEN; CHLOROXYLENOL; LANOLIN

Renew Periprotect

Active Ingredients:

Zinc Oxide 12%

Dimethicone 1%

Purpose:

Skin Protectant

Uses:

- Helps treat and prevent diaper rash.
- Protects minor skin irritation associated with

diaper rash and helps seal out wetness.

Warnings:

- For external use only,
- Avoid contact with eyes, In case of contact, flush thoroughly with water.

Warnings:

Stop use and ask a doctor If

• condition worsens
• symptoms last more than 7 days or clear up and
occur again within a few days.

Warnings:

Keep out of reach of children.

In case of accidental ingestion contact a physician or Poison Control Center right away.

Directions:

- Change wet and soiled diapers promptly, cleanse the diaper area and allow to dry.
- Apply cream liberally as often as necessary, with each diaper change, especially at bedtime or anytime when exposure to wet diapers may be prolonged.

Other Information:

- Store at room temperature (59º-86ºF)
- You may report a serious adverse event to DermaRite Industries, PO Box 7209, North Bergen, NJ 07047.

Inactive Ingredients:

Aloe Barbadensis Leaf Juice, Aluminum Stearate, Beeswax, Cholecalciferol, Chloroxylenol, Corn Oil, Imidazolidinyl Urea, Fragrance, Lanolin, Methylparaben, Mineral Oil, Paraffin Wax, Petrolatum, Phenoxyethanol, Propylene Glycol, Propylparaben, Retinyl Palmitate, Sorbitan Sesquioleate, Tocopheryl Acetate, Water.

Questions?

Call 800-337-6296 Mon - Fri 9AM - 5PM EST.